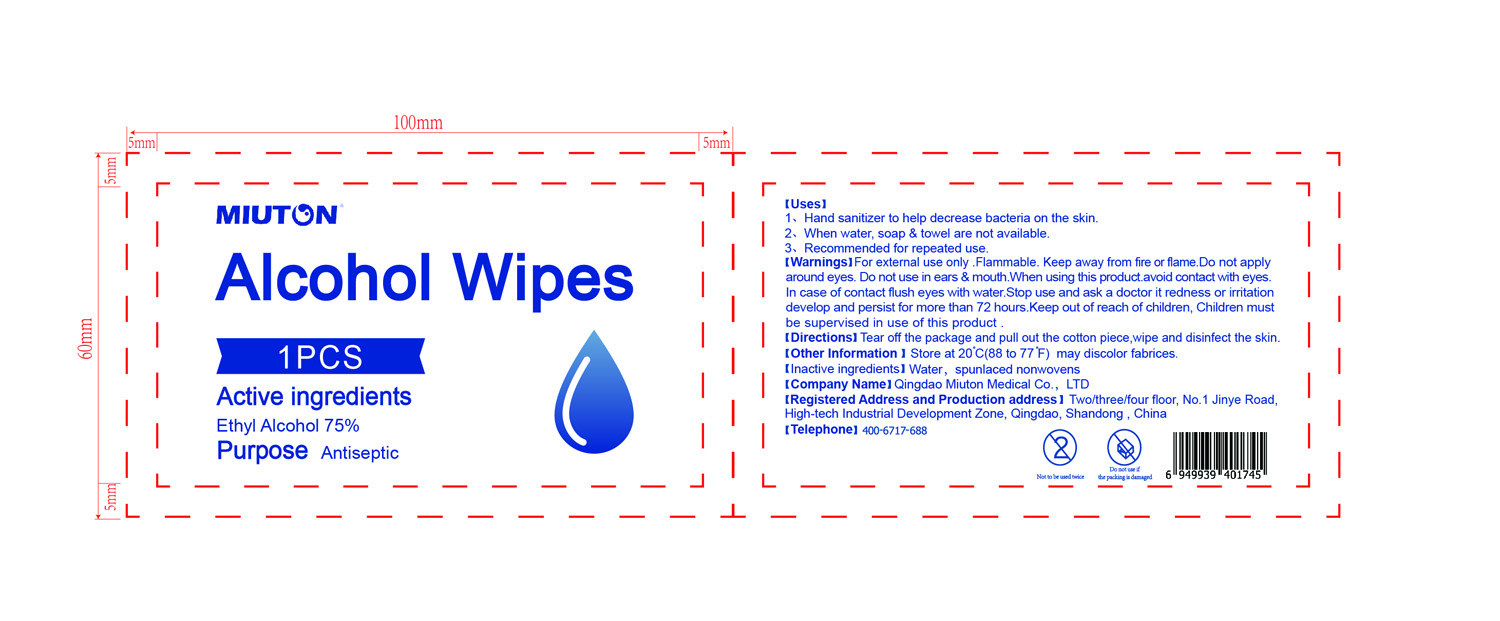 DRUG LABEL: Alcohol Wipes
NDC: 90059-001 | Form: CLOTH
Manufacturer: Qingdao Miuton Medical Co.,LTD.
Category: otc | Type: HUMAN OTC DRUG LABEL
Date: 20200804

ACTIVE INGREDIENTS: ALCOHOL 750 mL/1000 mL
INACTIVE INGREDIENTS: WATER

Drug Facts

Active Ingredient(s)

Ethyl Alcohol 75%

Purpose

Antiseptic

Use

1.Hand Sanitizer to help decrease bacteria on the skin.

2.When water,soap & towel are not available.

3.Recommended for repeated use.

Warnings

For external use only. Flammable. Keep away from fire or flame.

Do not use

Do not apply around eyes.

Do not use in ears & mouth.

When using this product avoid contact with eyes.In case of contact flush eyes with water.

Stop use and ask a doctor if redness or irritation develop and persist for more than 72 hours.

Keep out of reach of children. Children must be supervised in use of this product.

Directions

Tear off the package and pull out the cotton piece, wipe and disinfect the skin.

Other information

Store at 20C (88 to 77F) may discolor fabrices.

Inactive ingredients

Water, spunlaced nonwovens.